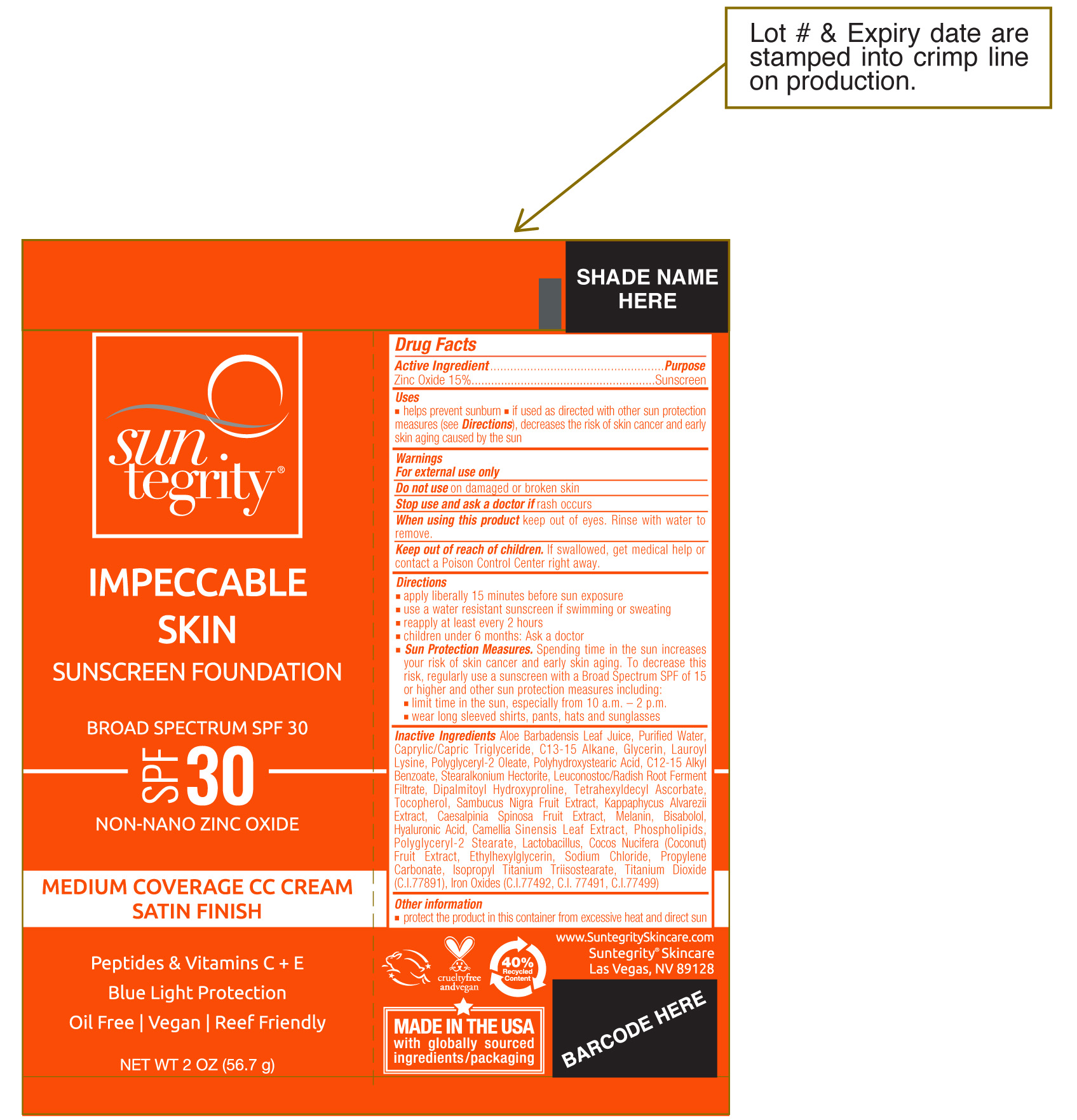 DRUG LABEL: Impeccable Skin Sunscreen Foundation Broad Spectrum SPF 30 Tan
NDC: 56152-0260 | Form: CREAM
Manufacturer: Cosmetic Enterprises Ltd
Category: otc | Type: HUMAN OTC DRUG LABEL
Date: 20251014

ACTIVE INGREDIENTS: ZINC OXIDE 15 g/100 g
INACTIVE INGREDIENTS: TARA SPINOSA FRUIT; C12-15 ALKYL BENZOATE; COCONUT; GLYCERIN; POLYGLYCERYL-2 OLEATE; POLYHYDROXYSTEARIC ACID (2300 MW); WATER; LACTOBACILLUS; ALOE BARBADENSIS LEAF; ISOPROPYL TITANIUM TRIISOSTEARATE; FERROSOFERRIC OXIDE; LEUCONOSTOC/RADISH ROOT FERMENT FILTRATE; TETRAHEXYLDECYL ASCORBATE; KAPPAPHYCUS ALVAREZII; TITANIUM DIOXIDE; DIPALMITOYL HYDROXYPROLINE; EUROPEAN ELDERBERRY; FERRIC OXIDE YELLOW; FERRIC OXIDE RED; SODIUM CHLORIDE; PROPYLENE CARBONATE; LAUROYL LYSINE; MELANIN SYNTHETIC (TYROSINE, PEROXIDE); EGG PHOSPHOLIPIDS; C13-15 ALKANE; TOCOPHEROL; POLYGLYCERYL-2 STEARATE; MEDIUM-CHAIN TRIGLYCERIDES; STEARALKONIUM HECTORITE; BISABOLOL; HYALURONIC ACID; GREEN TEA LEAF; ETHYLHEXYLGLYCERIN

Impeccable Skin Sunscreen Foundation Broad Spectrum SPF 30 Tan

Active ingredient.....Purpose

Zinc Oxide 15%......Sunscreen

Uses

- helps prevent sunburn
- if used as directed with other sun protection measures (see Directions), decreases the risk of skin cancer and early skin aging caused by the sun

Keep out of reach of children. If swallowed, get medical help or contact a Poison Control Center right away.

Stop use and ask a doctor if rash occurs

Warnings

For external use only

Do not use on damaged or broken skin

When using this product keep out of eyes. RInse with water to remove.

Directions

- apply liberally 15 minutes before sun exposure
- use a water resistant sunscreen if swimming or sweating
- reapply at least every 2 hours
- children under 6 months: Ask a doctor
- Sun Protection Measures. Spending time in the sun increases your risk of skin cancer and early skin aging. To decrease this risk regularly use a sunscreen with a Broad Spectrum SPF of 15 or higher and other sun protection measures including:
- limit time in the sun, especially from 10 a.m.-2 p.m.
- wear long sleeved shirts, pants, hats and sunglasses

INACTIVE INGREDIENT

Inactive Ingredients Aloe Barbadensis Leaf Juice, Purified Water, Caprylic/Capric Triglyceride, C13-15 Alkane, Glycerin, Lauroyl Lysine, Polyglyceryl-2 Oleate, Polyhydroxystearic Acid, C12-15 Alkyl Benzoate, Stearalkonium Hectorite, Leuconostoc/Radish Root Ferment Filtrate, Dipalmitoyl Hydroxyproline, Tetrahexyldecyl Ascorbate, Tocopherol, Sambucus Nigra Fruit Extract, Kappaphycus Alvarezii Extract, Caesalpinia Spinosa Fruit Extract, Melanin, Bisabolol, Hyaluronic Acid, Camellia Sinensis Leaf Extract, Phospholipids, Polyglyceryl-2 Stearate, Lactobacillus, Cocos Nucifera (Coconut) Fruit Extract, Ethylhexylglycerin, Sodium Chloride, Propylene Carbonate, Isopropyl Titanium, Triisostearate, Titanium Dioxide (C.I. 77891) Iron Oxides (C.I. 77492, C.I. 77491, C.I. 77499)

PACKAGE LABEL

Suntegrity

Impeccable Skin

Sunscreen Foundation

Broad Spectrum SPF 30

Non-Nano Zinc Oxide

Medium Coverage CC Cream Satin Finish

NET WT 2 OZ (56.7 g)